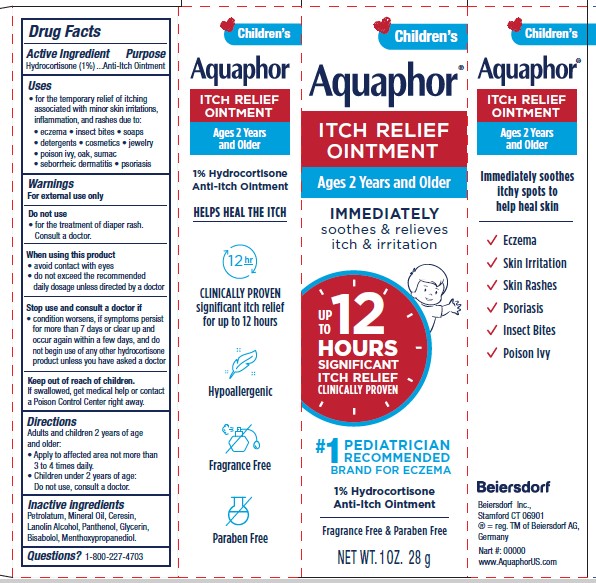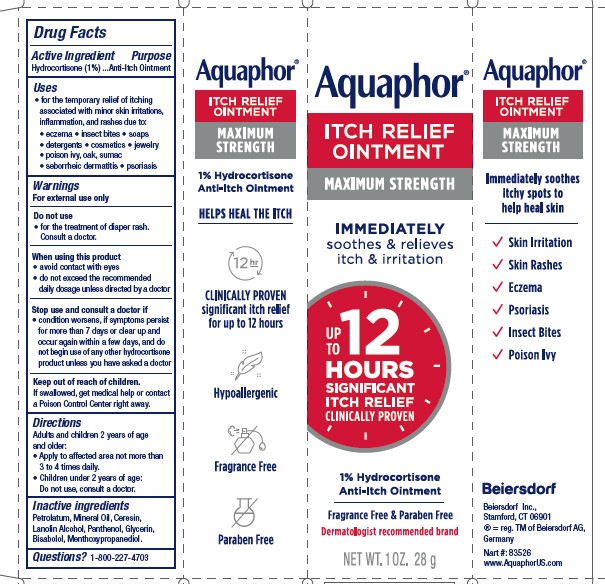 DRUG LABEL: Aquaphor Itch Relief
NDC: 10356-120 | Form: OINTMENT
Manufacturer: Beiersdorf Inc
Category: otc | Type: HUMAN OTC DRUG LABEL
Date: 20251216

ACTIVE INGREDIENTS: HYDROCORTISONE 1 g/100 g
INACTIVE INGREDIENTS: 3-((L-MENTHYL)OXY)PROPANE-1,2-DIOL; MINERAL OIL; CERESIN; LANOLIN ALCOHOLS; GLYCERIN; PANTHENOL; LEVOMENOL; PETROLATUM

Aquaphor Itch Relief Ointment

Active Ingredient

Hydrocortisone 1%

Purpose

Anti-Itch Ointment

Uses

• for the temporary relief of itching associated with minor skin irritations, inflammation, and rashes due to:

• eczema
• insect bites
• soaps
• poison ivy, oak, sumac
• seborrheic dermatitis
• psoriasis
• detergents
• cosmetics
• jewelry

Warnings

For external use only

Do not use
• for the treatment of diaper rash. Consult a doctor.

When using this product
• avoid contact with eyes
• do not exceed the recommended daily dosage unless directed by a doctor

Stop use and consult a doctor if
• condition worsens, if symptoms persist for more than 7 days or clear
up and occur again within a few days,

and do not begin use of any other hydrocortisone product unless you have asked a doctor

Keep out of reach of children. If swallowed, get medical help
or contact a Poison Control Center right away.

Directions
Adults and children 2 years of age and older:
• Apply to affected area not more than 3 to 4 times daily.
Children under 2 years of age: Do not use, consult a doctor.

Inactive ingredients

Petrolatum, Mineral Oil, Ceresin, Lanolin Alcohol,
Panthenol, Glycerin, Bisabolol, Menthoxypropanediol

Questions or comments?
1-800-227-4703

PACKAGE LABEL

Aquaphor Itch Relief Ointment

Maximum Strength

Immediately Soothes & Relieves Itch & Irritiation

Up to 12 hours Significant Itch Relief

Clinically Proven

1% Hydrocortisone Anti-Itch Ointment

Dermatologist Recommended Brand

Fragrance free and Paraben free

Hypoallergenic

Helps Heal the Itch

Clinically proven significant itch relief for up to 12 hours

Immediately soothes itchy spots to help skin heal

Skin irritation

Skin rashes

Eczema

Psoriasis

Eczema

Poison Ivy

Children's

Aquaphor Itch Relief Ointment

Ages 2 Years and Older

Immediately Soothes & Relieves Itch & Irritiation

Up to 12 hours Significant Itch Relief

Clinically Proven

Number 1 Pediatrician Recommended Brand for Eczema

1% Hydrocortisone Anti-Itch Ointment

Dermatologist Recommended Brand

Fragrance free and Paraben free

Hypoallergenic

Helps Heal the Itch

Clinically proven significant itch relief for up to 12 hours

Immediately soothes itchy spots to help skin heal

Eczema

Skin irritation

Skin rashes

Psoriasis

Eczema

Poison Ivy